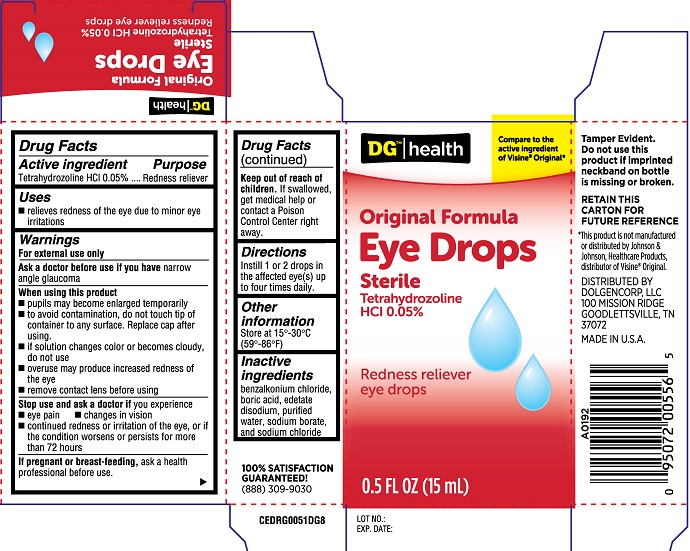 DRUG LABEL: DG Original Eye Drops
NDC: 55910-363 | Form: SOLUTION
Manufacturer: Dolgencorp LLC
Category: otc | Type: HUMAN OTC DRUG LABEL
Date: 20251230

ACTIVE INGREDIENTS: TETRAHYDROZOLINE HYDROCHLORIDE 0.05 g/100 mL
INACTIVE INGREDIENTS: BENZALKONIUM CHLORIDE; BORIC ACID; WATER; SODIUM BORATE; EDETATE DISODIUM; SODIUM CHLORIDE

DG Original Eye Drops (PLD)

Active ingredient

Tetrahydrozoline HCl 0.05%

Purpose

Tetrahydrozoline HCl......Redness reliever

Uses

- relieves redness of the eye due to minor eye irritations

Warnings

For external use only

Ask a doctor before use if you have narrow angle glaucoma

When using this product

- pupils may become enlarged temporarily
- to avoid contamination, do not touch tip of container to any surface. Replace cap after using
- if solution changes color or becomes cloudy, do not use
- overuse may produce increased redness of the eye
- remove contact lens before using

Stop use and ask a doctor if you experience

- eye pain
- changes in vision
- coontinued redness or irritation of the eye, or if the condition worsens or persists for more than 72 hours

PREGNANCY OR BREAST FEEDING

If pregnant or breast-feeding, ask a health professional before use

Keep out of reach of children. If swallowed, get medical help or contact a Poison Control Center right away.

Directions

Instill 1 or 2 drops in the affected eye(s) up to four times daily.

Other information

Store at 15º-30ºC (59º-86ºF)

Inactive ingredients

benzalkonium chloride, boric acid, edetate disodium, purified water, sodium borate, and sodium chloride